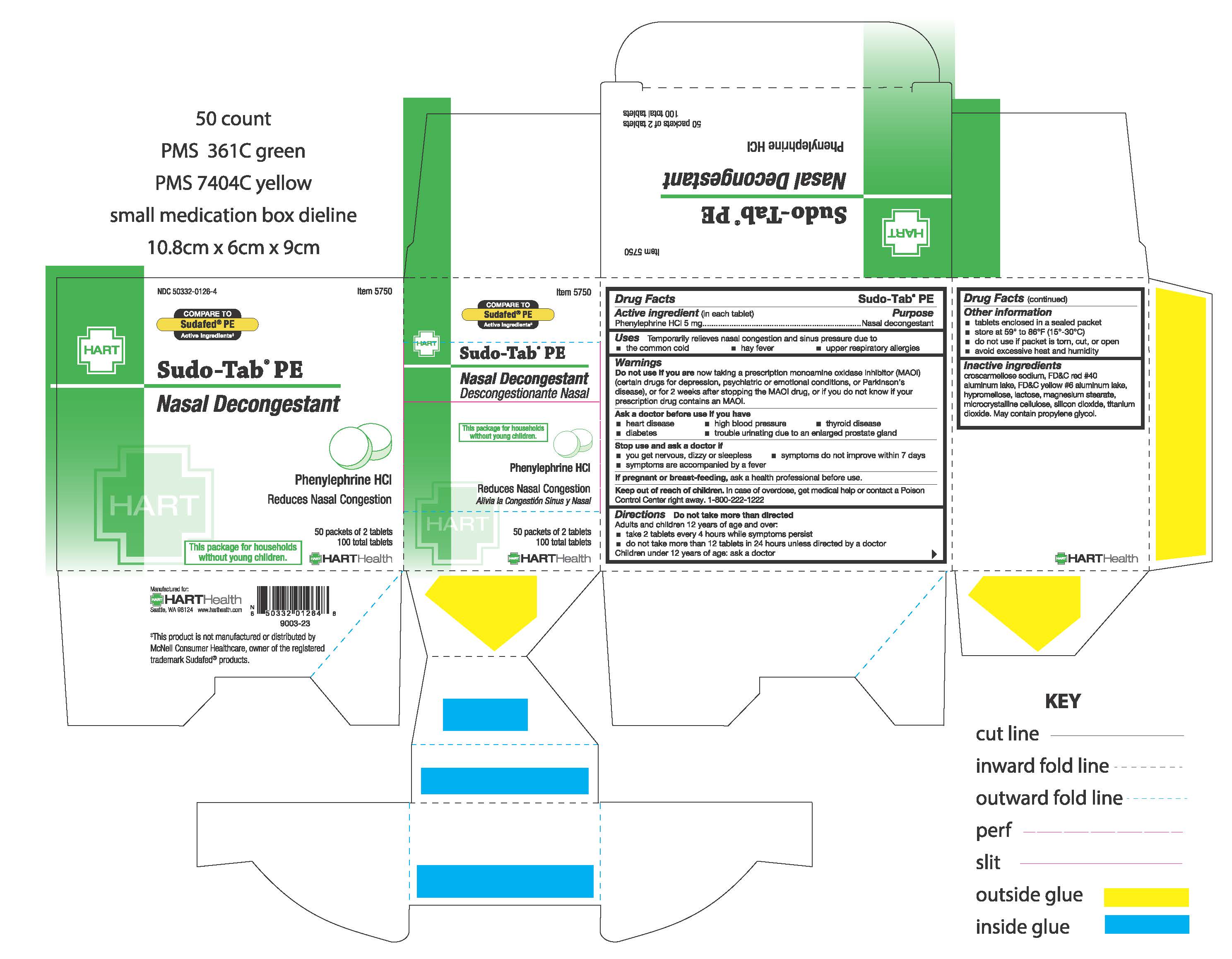 DRUG LABEL: Sudo-Tab PE
NDC: 50332-0126 | Form: TABLET
Manufacturer: HART Health
Category: otc | Type: HUMAN OTC DRUG LABEL
Date: 20241203

ACTIVE INGREDIENTS: PHENYLEPHRINE HYDROCHLORIDE 5 mg/1 1
INACTIVE INGREDIENTS: CROSCARMELLOSE SODIUM; FD&C RED NO. 40; FD&C YELLOW NO. 6; LACTOSE; MAGNESIUM STEARATE; CELLULOSE, MICROCRYSTALLINE; PROPYLENE GLYCOL; SILICON DIOXIDE; TITANIUM DIOXIDE

SUDO-TAB PE

Active Ingredient (in each tablet): Phenylephrine HCl 5mg

Purpose:

Nasal Decongestant

INDICATIONS AND USAGE

Uses: Temporarily relieves nasal congestion and sinus pressure due to

- the common cold
- hay fever
- upper respiratory allergies

Warnings:

Do not use if you are now taking a prescription monoamine oxidase inhibitor (MAOI) (certain drugs for depression, psychiatric or emotional conditions, or Parkinson's disease), for 2 weeks after stopping the MAOI drug, or if you do not know if your prescription drug contains and MAOI.

Ask a doctor before use if you have

- heart disease
- high blood pressure
- thyroid disease
- diabetes
- trouble urinating due to an enlarged prostate gland

Stop use and ask a doctor if

- you get nervous, dizzy or sleepless
- symptoms do not improve within 7 days
- symptoms are accompanied by a fever

PREGNANCY OR BREAST FEEDING

If pregnant or breast-feeding, ask a health professional before use

Keep out of reach of children. In case of overdose, get medical help or contact a Poison Control Center right away. 1-800-222-1222

Directions:

Do not take more than directed

Adults and children 12 years of age and over:

- take 2 tablets every 4 hours while symptoms persist
- do not take more than 12 tablets in 24 hours unless directed by a doctor

Children under 12 years of age: ask a doctor

Other information

■ tablets enclosed in a sealed packet

■ do not use if packet is torn, cut or open

■ store at 59° to 86°F (15°-30°C)

■ avoid excessive heat and humidity

INACTIVE INGREDIENT

Inactive Ingredients: croscarmellose sodium, FD&C red #40 aluminum lake, FD&C yellow #6 aluminum lake, hypromellose, lactose, magnesium stearate, microcrystalline cellulose, silicon dioxide, titanium dioxide. May contain propylene glycol.